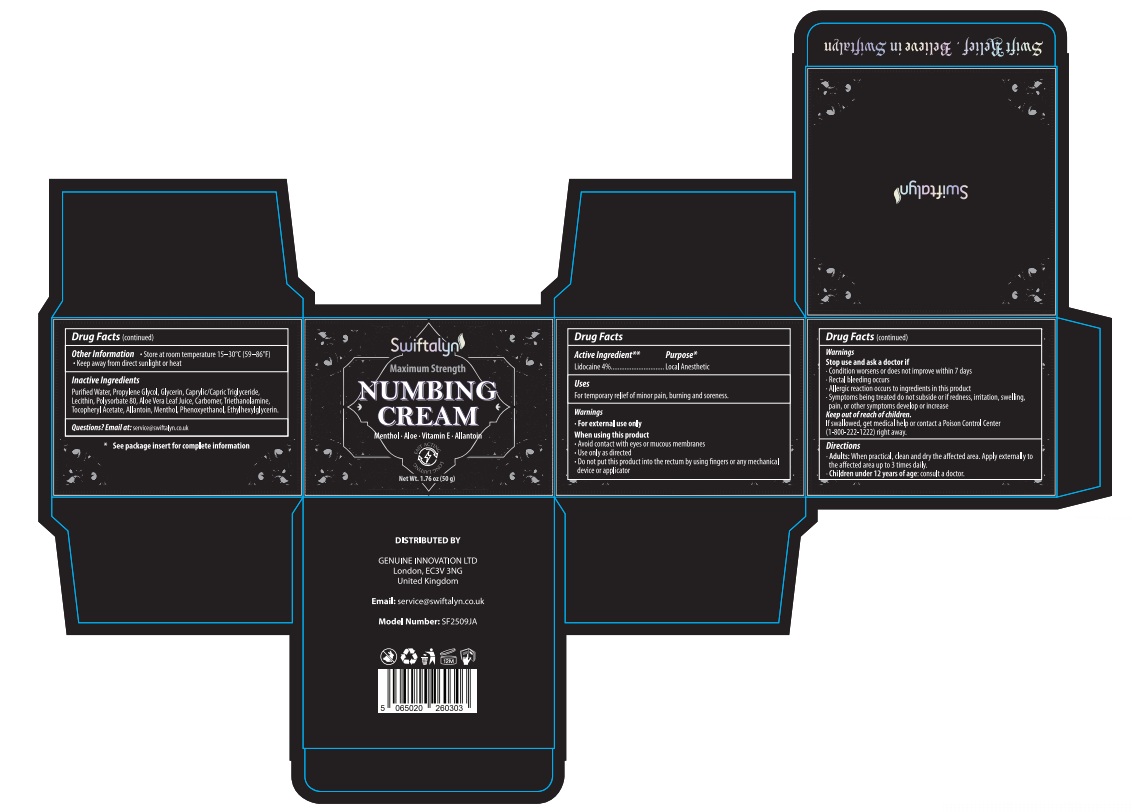 DRUG LABEL: Swiftalyn Numbing Cream
NDC: 87013-002 | Form: CREAM
Manufacturer: GENUINE INNOVATION LTD
Category: otc | Type: HUMAN OTC DRUG LABEL
Date: 20260212

ACTIVE INGREDIENTS: LIDOCAINE 4 g/100 g
INACTIVE INGREDIENTS: MENTHOL; POLYSORBATE 80; GLYCERIN; SOYBEAN LECITHIN; PROPYLENE GLYCOL; TROLAMINE; ALOE VERA LEAF JUICE; PHENOXYETHANOL; CAPRYLIC/CAPRIC TRIGLYCERIDE; ALLANTOIN; ETHYLHEXYLGLYCERIN; CARBOMER; ALPHA-TOCOPHEROL ACETATE; WATER

ACTIVE INGREDIENT

Lidocaine 4%

PURPOSE

For temporary relief of minor pain, burning and soreness.

INDICATIONS AND USAGE

For use as a local anesthetic to numb the skin prior to minor medical or cosmetic procedures

WARNINGS

For external use only

WHEN USING

■ avoid contact with eyes or mucous membranes ■ Use only as directed ■ do not put this product into the rectum by using fingers or any mechanical device or applicator

STOP USE

■ condition worsens or does not improve within 7 days ■ rectal bleeding occurs ■ allergic reaction occurs to ingredients in this product ■ symptoms being treated do not subside or if redness, irritation, swelling, pain, or other symptoms develop or increase

KEEP OUT OF REACH OF CHILDREN

If swallowed, get medical help or contact a Poison Control Center (1-800-222-1222) right away.

DOSAGE AND ADMINISTRATION

■ Adults: When practical, clean and dry the affected area. Apply externally to the affected area up to 3 times daily. ■ Children under 12 years of age: consult a doctor.

OTHER SAFETY INFORMATION

■ Store at room temperature 15–30°C (59–86°F) ■ Keep away from direct sunlight or heat

INACTIVE INGREDIENT

Purified Water, Propylene Glycol, Glycerin, Caprylic/Capric Triglyceride, Lecithin, Polysorbate 80, Aloe Vera Leaf Juice, Carbomer, Triethanolamine, Tocopheryl Acetate, Allantoin, Menthol, Phenoxyethanol, Ethylhexylglycerin.

QUESTIONS

Email at:

service@swiftalyn.co.uk